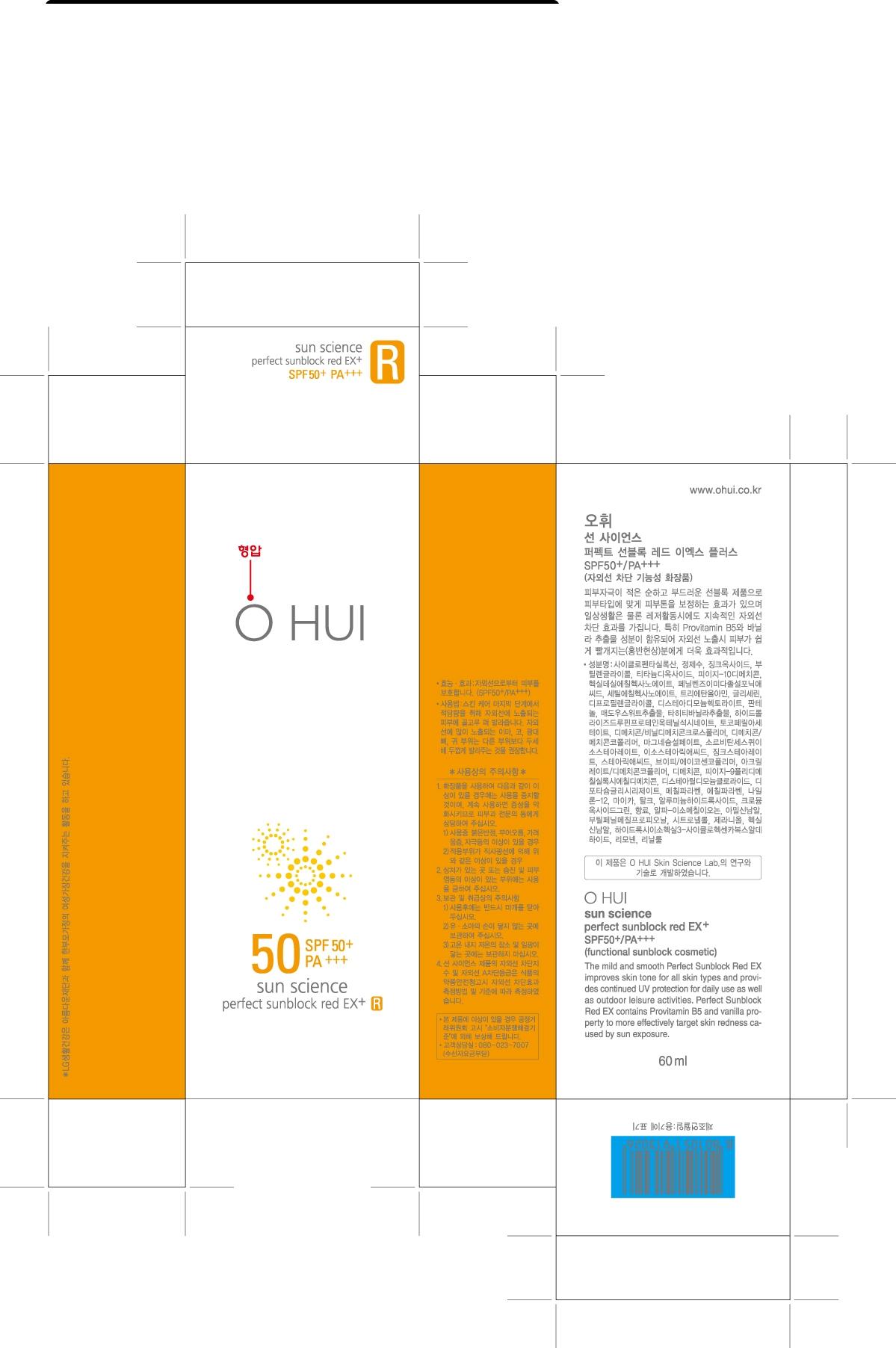 DRUG LABEL: OHUI SUN SCIENCE PERFECT SUNBLOCK RED EX
NDC: 53208-494 | Form: CREAM
Manufacturer: LG Household and Healthcare, Inc.
Category: otc | Type: HUMAN OTC DRUG LABEL
Date: 20101216

ACTIVE INGREDIENTS: ZINC OXIDE 13.34 mL/100 mL; TITANIUM DIOXIDE 7 mL/100 mL
INACTIVE INGREDIENTS: DIMETHICONE; WATER; CYCLOMETHICONE 5; METHYLPARABEN; BUTYLENE GLYCOL; VANILLA; CETYL ETHYLHEXANOATE; GLYCERIN; DIPROPYLENE GLYCOL; HEXYL LAURATE; FRUIT; MAGNESIUM SULFATE, UNSPECIFIED; HECTORITE; ALUMINUM OXIDE; ZINC STEARATE; SORBITAN; PANTHENOL; ISOSTEARIC ACID; ENSULIZOLE; TROLAMINE; DISTEARYLDIMONIUM CHLORIDE; TALC; ETHYLPARABEN; MICA; CHROMIUM

Drug Facts

ACTIVE INGREDIENT

ZINC OXIDE 13.34%

TITANIUM DIOXIDE 7%

WARNINGS AND PRECAUTIONS

For external use only.

Keep out of reach of children

If swallowed, get medical help or contact a Poison Control Center right away.

STOP USE

Stop use if a rash or irritation develops and lasts.

WHEN USING

Keep out of eyes. Rinse with water to remove.

PACKAGE LABEL

Ohui Sun Perfect Red EX